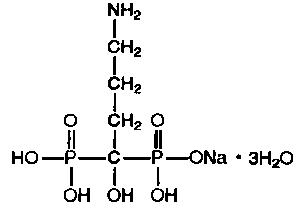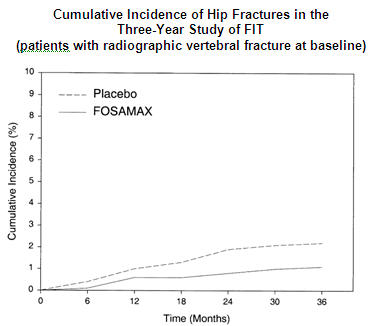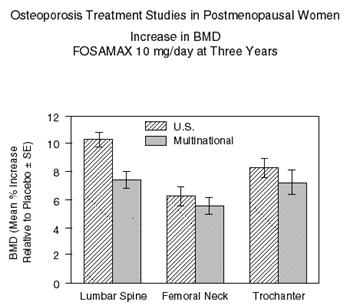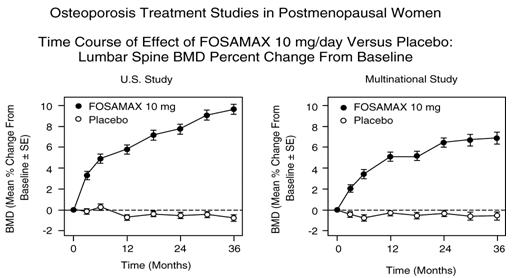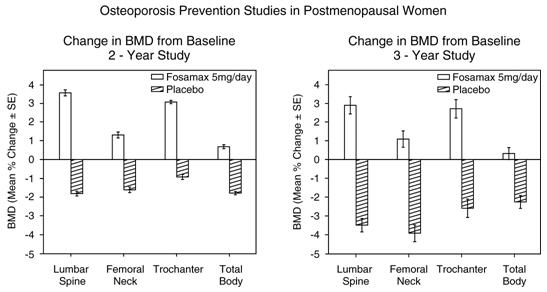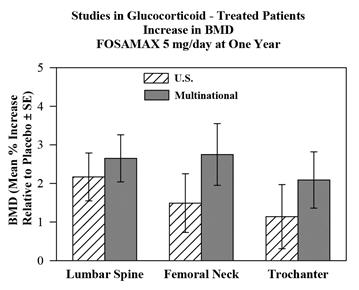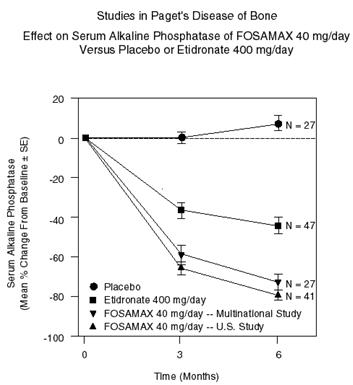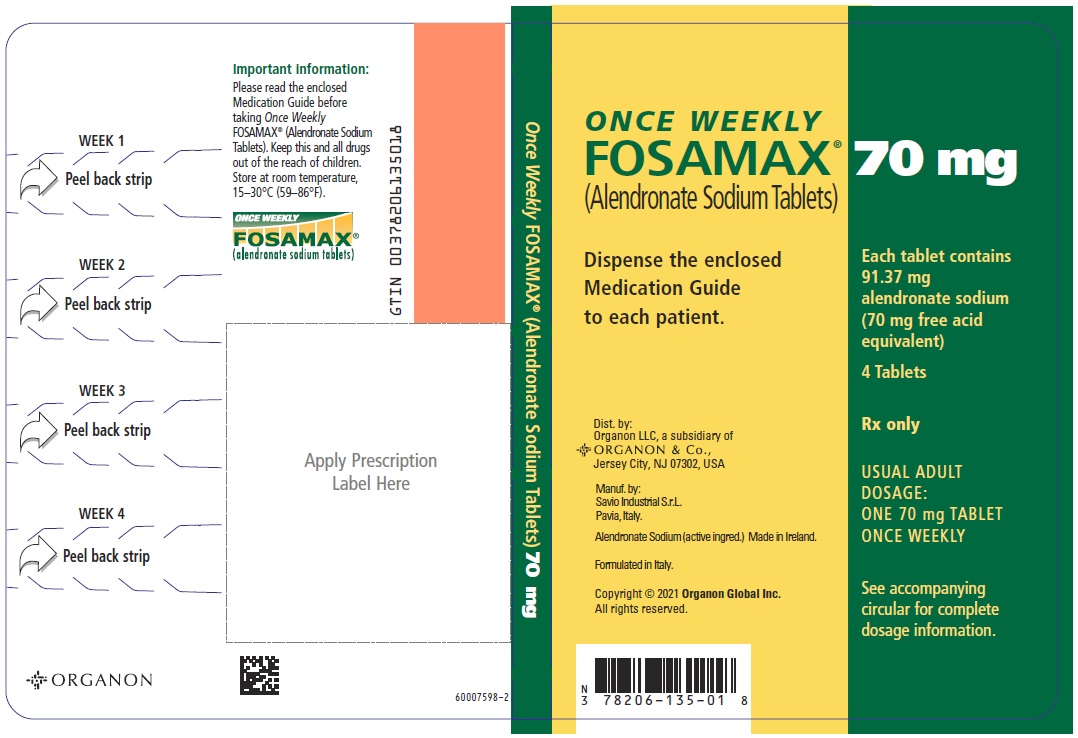 DRUG LABEL: FOSAMAX
NDC: 78206-135 | Form: TABLET
Manufacturer: Organon LLC
Category: prescription | Type: HUMAN PRESCRIPTION DRUG LABEL
Date: 20260203

ACTIVE INGREDIENTS: ALENDRONATE SODIUM 70 mg/1 1
INACTIVE INGREDIENTS: MICROCRYSTALLINE CELLULOSE; ANHYDROUS LACTOSE; CROSCARMELLOSE SODIUM; MAGNESIUM STEARATE

HIGHLIGHTS OF PRESCRIBING INFORMATION

These highlights do not include all the information needed to use FOSAMAX safely and effectively. See full prescribing information for FOSAMAX.
FOSAMAX® (alendronate sodium) tablets, for oral use
FOSAMAX® (alendronate sodium) oral solution
Initial U.S. Approval: 1995

RECENT MAJOR CHANGES

Warnings and Precautions, Atypical Fractures Including Femoral Fractures (5.5) | 2/2026

1 INDICATIONS AND USAGE

FOSAMAX is a bisphosphonate indicated for:

- Treatment and prevention of osteoporosis in postmenopausal women (1.1, 1.2)
- Treatment to increase bone mass in men with osteoporosis (1.3)
- Treatment of glucocorticoid-induced osteoporosis (1.4)
- Treatment of Paget's disease of bone (1.5)

Limitations of use:
Optimal duration of use has not been determined. For patients at low-risk for fracture, consider drug discontinuation after 3 to 5 years of use. (1.6)

2 DOSAGE AND ADMINISTRATION

- Treatment of osteoporosis in postmenopausal women and in men: 10 mg daily or 70 mg (tablet or oral solution) once weekly. (2.1, 2.3)
- Prevention of osteoporosis in postmenopausal women: 5 mg daily or 35 mg once weekly. (2.2)
- Glucocorticoid-induced osteoporosis: 5 mg daily; or 10 mg daily in postmenopausal women not receiving estrogen. (2.4)
- Paget's disease: 40 mg daily for six months. (2.5)
- Instruct patients to: (2.6)
  - Swallow tablets whole with 6-8 ounces plain water at least 30 minutes before the first food, drink, or medication of the day.
  - Swallow oral solution followed by at least 2 ounces of water.
  - Not lie down for at least 30 minutes after taking FOSAMAX and until after food.

3 DOSAGE FORMS AND STRENGTHS

Tablets: 70 mg (3)

4 CONTRAINDICATIONS

- Abnormalities of the esophagus which delay emptying such as stricture or achalasia (4, 5.1)
- Inability to stand/sit upright for at least 30 minutes (2.6, 4, 5.1)
- Do not administer FOSAMAX oral solution to patients at increased risk of aspiration (4)
- Hypocalcemia (4, 5.2)
- Hypersensitivity to any component of this product (4, 6.2)

5 WARNINGS AND PRECAUTIONS

- Upper Gastrointestinal Adverse Reactions can occur. Instruct patients to follow dosing instructions. Discontinue if new or worsening symptoms occur. (5.1)
- Hypocalcemia can worsen and must be corrected prior to use. (5.2)
- Severe Bone, Joint, Muscle Pain may occur. Discontinue use if severe symptoms develop. (5.3)
- Osteonecrosis of the Jaw has been reported. (5.4)
- Atypical Fractures Including Femoral Fractures have been reported. Patients with new thigh or groin pain should be evaluated to rule out a femoral fracture. Risk/benefit of continuing bisphosphonate therapy should be re-evaluated in these patients and interruption of bisphosphonate therapy should be considered (5.5)

6 ADVERSE REACTIONS

Most common adverse reactions (greater than or equal to 3%) are abdominal pain, acid regurgitation, constipation, diarrhea, dyspepsia, musculoskeletal pain, nausea. (6.1)

To report SUSPECTED ADVERSE REACTIONS, contact Organon LLC, a subsidiary of Organon & Co., at 1-844-674-3200 or FDA at 1-800-FDA-1088 or www.fda.gov/medwatch.

7 DRUG INTERACTIONS

- Calcium supplements, antacids, or oral medications containing multivalent cations interfere with absorption of alendronate. (2.6, 7.1)
- Use caution when co-prescribing aspirin/nonsteroidal anti-inflammatory drugs that may worsen gastrointestinal irritation. (7.2, 7.3)

8 USE IN SPECIFIC POPULATIONS

- Pregnancy: Discontinue when pregnancy is recognized. (8.1)
- FOSAMAX is not indicated for use in pediatric patients. (8.4)
- FOSAMAX is not recommended in patients with renal impairment (creatinine clearance less than 35 mL/min). (5.6, 8.6)

FULL PRESCRIBING INFORMATION

1 INDICATIONS AND USAGE

1.1 Treatment of Osteoporosis in Postmenopausal Women

FOSAMAX® is indicated for the treatment of osteoporosis in postmenopausal women. In postmenopausal women, FOSAMAX increases bone mass and reduces the incidence of fractures, including those of the hip and spine (vertebral compression fractures). [See Clinical Studies (14.1).]

1.2 Prevention of Osteoporosis in Postmenopausal Women

FOSAMAX is indicated for the prevention of postmenopausal osteoporosis [see Clinical Studies (14.2)].

1.3 Treatment to Increase Bone Mass in Men with Osteoporosis

FOSAMAX is indicated for treatment to increase bone mass in men with osteoporosis [see Clinical Studies (14.3)].

1.4 Treatment of Glucocorticoid-Induced Osteoporosis

FOSAMAX is indicated for the treatment of glucocorticoid-induced osteoporosis in men and women receiving glucocorticoids in a daily dosage equivalent to 7.5 mg or greater of prednisone and who have low bone mineral density [see Clinical Studies (14.4)].

1.5 Treatment of Paget's Disease of Bone

FOSAMAX is indicated for the treatment of Paget's disease of bone in men and women. Treatment is indicated in patients with Paget's disease of bone who have alkaline phosphatase at least two times the upper limit of normal, or those who are symptomatic, or those at risk for future complications from their disease. [See Clinical Studies (14.5).]

1.6 Important Limitations of Use

The optimal duration of use has not been determined. The safety and effectiveness of FOSAMAX for the treatment of osteoporosis are based on clinical data of four years duration. All patients on bisphosphonate therapy should have the need for continued therapy re-evaluated on a periodic basis. Patients at low-risk for fracture should be considered for drug discontinuation after 3 to 5 years of use. Patients who discontinue therapy should have their risk for fracture re-evaluated periodically.

2 DOSAGE AND ADMINISTRATION

Although alendronate tablets 5 mg, 10 mg, 35 mg, and 40 mg are available in the marketplace, FOSAMAX is no longer marketed in the 5 mg, 10 mg, 35 mg, and 40 mg strengths.

Although an oral solution of alendronate may be available in the marketplace, FOSAMAX oral solution is no longer marketed.

2.1 Treatment of Osteoporosis in Postmenopausal Women

The recommended dosage is:

- one 70 mg tablet once weekly
  or
- one bottle of 70 mg oral solution once weekly
  or
- one 10 mg tablet once daily

2.2 Prevention of Osteoporosis in Postmenopausal Women

The recommended dosage is:

- one 35 mg tablet once weekly
  or
- one 5 mg tablet once daily

2.3 Treatment to Increase Bone Mass in Men with Osteoporosis

The recommended dosage is:

- one 70 mg tablet once weekly
  or
- one bottle of 70 mg oral solution once weekly
  or
- one 10 mg tablet once daily

2.4 Treatment of Glucocorticoid-Induced Osteoporosis

The recommended dosage is one 5 mg tablet once daily, except for postmenopausal women not receiving estrogen, for whom the recommended dosage is one 10 mg tablet once daily.

2.5 Treatment of Paget's Disease of Bone

The recommended treatment regimen is 40 mg once a day for six months.

Re-treatment of Paget's Disease

Re-treatment with FOSAMAX may be considered, following a six-month post-treatment evaluation period in patients who have relapsed, based on increases in serum alkaline phosphatase, which should be measured periodically. Re-treatment may also be considered in those who failed to normalize their serum alkaline phosphatase.

2.6 Important Administration Instructions

Instruct patients to do the following:

- Take FOSAMAX at least one-half hour before the first food, beverage, or medication of the day with plain water only [see Patient Counseling Information (17)]. Other beverages (including mineral water), food, and some medications are likely to reduce the absorption of FOSAMAX [see Drug Interactions (7.1)]. Waiting less than 30 minutes, or taking FOSAMAX with food, beverages (other than plain water) or other medications will lessen the effect of FOSAMAX by decreasing its absorption into the body.
- Take FOSAMAX upon arising for the day. To facilitate delivery to the stomach and thus reduce the potential for esophageal irritation, a FOSAMAX tablet should be swallowed with a full glass of water (6-8 ounces). To facilitate gastric emptying FOSAMAX oral solution should be followed by at least 2 ounces (a quarter of a cup) of water. Patients should not lie down for at least 30 minutes and until after their first food of the day. FOSAMAX should not be taken at bedtime or before arising for the day. Failure to follow these instructions may increase the risk of esophageal adverse experiences [see Warnings and Precautions (5.1) and Patient Counseling Information (17)].

2.7 Recommendations for Calcium and Vitamin D Supplementation

Instruct patients to take supplemental calcium if dietary intake is inadequate [see Warnings and Precautions (5.2)]. Patients at increased risk for vitamin D insufficiency (e.g., over the age of 70 years, nursing home-bound, or chronically ill) may need vitamin D supplementation. Patients with gastrointestinal malabsorption syndromes may require higher doses of vitamin D supplementation and measurement of 25-hydroxyvitamin D should be considered.

Patients treated with glucocorticoids should receive adequate amounts of calcium and vitamin D.

2.8 Administration Instructions for Missed Doses

If a once-weekly dose of FOSAMAX is missed, instruct patients to take one dose on the morning after they remember. They should not take two doses on the same day but should return to taking one dose once a week, as originally scheduled on their chosen day.

3 DOSAGE FORMS AND STRENGTHS

- 70 mg tablets are white, oval, uncoated tablets with code 31 on one side and an outline of a bone image on the other.

4 CONTRAINDICATIONS

FOSAMAX is contraindicated in patients with the following conditions:

- Abnormalities of the esophagus which delay esophageal emptying such as stricture or achalasia [see Warnings and Precautions (5.1)]
- Inability to stand or sit upright for at least 30 minutes [see Dosage and Administration (2.6); Warnings and Precautions (5.1)]
- Do not administer FOSAMAX oral solution to patients at increased risk of aspiration.
- Hypocalcemia [see Warnings and Precautions (5.2)]
- Hypersensitivity to any component of this product. Hypersensitivity reactions including urticaria and angioedema have been reported [see Adverse Reactions (6.2)].

5 WARNINGS AND PRECAUTIONS

5.1 Upper Gastrointestinal Adverse Reactions

FOSAMAX, like other bisphosphonates administered orally, may cause local irritation of the upper gastrointestinal mucosa. Because of these possible irritant effects and a potential for worsening of the underlying disease, caution should be used when FOSAMAX is given to patients with active upper gastrointestinal problems (such as known Barrett's esophagus, dysphagia, other esophageal diseases, gastritis, duodenitis, or ulcers).

Esophageal adverse experiences, such as esophagitis, esophageal ulcers and esophageal erosions, occasionally with bleeding and rarely followed by esophageal stricture or perforation, have been reported in patients receiving treatment with oral bisphosphonates including FOSAMAX. In some cases these have been severe and required hospitalization. Physicians should therefore be alert to any signs or symptoms signaling a possible esophageal reaction and patients should be instructed to discontinue FOSAMAX and seek medical attention if they develop dysphagia, odynophagia, retrosternal pain or new or worsening heartburn.

The risk of severe esophageal adverse experiences appears to be greater in patients who lie down after taking oral bisphosphonates including FOSAMAX and/or who fail to swallow oral bisphosphonates including FOSAMAX with the recommended full glass (6-8 ounces) of water, and/or who continue to take oral bisphosphonates including FOSAMAX after developing symptoms suggestive of esophageal irritation. Therefore, it is very important that the full dosing instructions are provided to, and understood by, the patient [see Dosage and Administration (2.6)]. In patients who cannot comply with dosing instructions due to mental disability, therapy with FOSAMAX should be used under appropriate supervision.

There have been post-marketing reports of gastric and duodenal ulcers with oral bisphosphonate use, some severe and with complications, although no increased risk was observed in controlled clinical trials [see Adverse Reactions (6.2)].

5.2 Mineral Metabolism

Hypocalcemia must be corrected before initiating therapy with FOSAMAX [see Contraindications (4)]. Other disorders affecting mineral metabolism (such as vitamin D deficiency) should also be effectively treated. In patients with these conditions, serum calcium and symptoms of hypocalcemia should be monitored during therapy with FOSAMAX.

Presumably due to the effects of FOSAMAX on increasing bone mineral, small, asymptomatic decreases in serum calcium and phosphate may occur, especially in patients with Paget's disease, in whom the pretreatment rate of bone turnover may be greatly elevated, and in patients receiving glucocorticoids, in whom calcium absorption may be decreased.

Ensuring adequate calcium and vitamin D intake is especially important in patients with Paget's disease of bone and in patients receiving glucocorticoids.

5.3 Musculoskeletal Pain

In post-marketing experience, severe and occasionally incapacitating bone, joint, and/or muscle pain has been reported in patients taking bisphosphonates that are approved for the prevention and treatment of osteoporosis [see Adverse Reactions (6.2)]. This category of drugs includes FOSAMAX (alendronate). Most of the patients were postmenopausal women. The time to onset of symptoms varied from one day to several months after starting the drug. Discontinue use if severe symptoms develop. Most patients had relief of symptoms after stopping. A subset had recurrence of symptoms when rechallenged with the same drug or another bisphosphonate.

In placebo-controlled clinical studies of FOSAMAX, the percentages of patients with these symptoms were similar in the FOSAMAX and placebo groups.

5.4 Osteonecrosis of the Jaw

Osteonecrosis of the jaw (ONJ), which can occur spontaneously, is generally associated with tooth extraction and/or local infection with delayed healing, and has been reported in patients taking bisphosphonates, including FOSAMAX. Known risk factors for osteonecrosis of the jaw include invasive dental procedures (e.g., tooth extraction, dental implants, boney surgery), diagnosis of cancer, concomitant therapies (e.g., chemotherapy, corticosteroids, angiogenesis inhibitors), poor oral hygiene, and co-morbid disorders (e.g., periodontal and/or other pre-existing dental disease, anemia, coagulopathy, infection, ill-fitting dentures). The risk of ONJ may increase with duration of exposure to bisphosphonates.

For patients requiring invasive dental procedures, discontinuation of bisphosphonate treatment may reduce the risk for ONJ. Clinical judgment of the treating physician and/or oral surgeon should guide the management plan of each patient based on individual benefit/risk assessment.

Patients who develop osteonecrosis of the jaw while on bisphosphonate therapy should receive care by an oral surgeon. In these patients, extensive dental surgery to treat ONJ may exacerbate the condition. Discontinuation of bisphosphonate therapy should be considered based on individual benefit/risk assessment.

5.5 Atypical Fractures Including Femoral Fractures

Atypical, low-energy, or low trauma fractures of the femoral shaft have been reported during treatment with bisphosphonates, including alendronate, in patients with osteoporosis. Atypical femur and other fractures most commonly occur with minimal or no trauma to the affected area. These fractures occurred anywhere in the femoral shaft from just below the lesser trochanter to above the supracondylar flare and are transverse or short oblique in orientation without evidence of comminution. Atypical fractures of other bones have also been reported. They may be bilateral. There fractures can also occur in osteoporotic patients who have not been treated with bisphosphonates.Concomitant treatment with glucocorticoid may also induce these fractures.

Prodromal pain in the affected area, usually presenting as dull, aching thigh pain, weeks to months before a complete fracture occurs was reported by patients.

Any patient with a history of bisphosphonate exposure who presents with thigh or groin pain should be suspected of having an atypical fracture and should be evaluated to rule out an incomplete femur fracture. Bony pain in other locations should also be considered for evaluation of atypical fracture. Patients presenting with an atypical fracture should also be assessed for symptoms and signs of fracture in the contralateral limb. Risk/benefit of continuing bisphosphonate therapy should be re-evaluated in these patients and interruption of bisphosphonate therapy should be considered.

5.6 Renal Impairment

FOSAMAX is not recommended for patients with creatinine clearance less than 35 mL/min.

5.7 Glucocorticoid-Induced Osteoporosis

The risk versus benefit of FOSAMAX for treatment at daily dosages of glucocorticoids less than 7.5 mg of prednisone or equivalent has not been established [see Indications and Usage (1.4)]. Before initiating treatment, the gonadal hormonal status of both men and women should be ascertained and appropriate replacement considered.

A bone mineral density measurement should be made at the initiation of therapy and repeated after 6 to 12 months of combined FOSAMAX and glucocorticoid treatment.

6 ADVERSE REACTIONS

The following clinically significant adverse drug reactions are described elsewhere in the labeling:

- Upper Gastrointestinal Adverse Reactions [see Warnings and Precautions (5.1)]
- Mineral Metabolism [see Warnings and Precautions (5.2)]
- Musculoskeletal Pain [see Warnings and Precautions (5.3)]
- Osteonecrosis of the Jaw [see Warnings and Precautions (5.4)]
- Atypical Fractures Including Femoral Fractures [see Warnings and Precautions (5.5)]
- Renal Impairment [see Warnings and Precautions (5.6)]
- Glucocorticoid-Induced Osteoporosis [see Warnings and Precautions (5.7)]

6.1 Clinical Trials Experience

Because clinical trials are conducted under widely varying conditions, adverse reaction rates observed in the clinical trials of a drug cannot be directly compared to rates in the clinical trials of another drug and may not reflect the rates observed in clinical practice.

Treatment of Osteoporosis in Postmenopausal Women

Daily Dosing

The safety of FOSAMAX in the treatment of postmenopausal osteoporosis was assessed in four clinical trials that enrolled 7453 women aged 44-84 years. Study 1 and Study 2 were identically designed, three-year, placebo-controlled, double-blind, multicenter studies (United States and Multinational n=994); Study 3 was the three-year vertebral fracture cohort of the Fracture Intervention Trial [FIT] (n=2027) and Study 4 was the four-year clinical fracture cohort of FIT (n=4432). Overall, 3620 patients were exposed to placebo and 3432 patients exposed to FOSAMAX. Patients with pre-existing gastrointestinal disease and concomitant use of non-steroidal anti-inflammatory drugs were included in these clinical trials. In Study 1 and Study 2 all women received 500 mg elemental calcium as carbonate. In Study 3 and Study 4 all women with dietary calcium intake less than 1000 mg per day received 500 mg calcium and 250 international units Vitamin D per day.

Among patients treated with alendronate 10 mg or placebo in Study 1 and Study 2, and all patients in Study 3 and Study 4, the incidence of all-cause mortality was 1.8% in the placebo group and 1.8% in the FOSAMAX group. The incidence of serious adverse event was 30.7% in the placebo group and 30.9% in the FOSAMAX group. The percentage of patients who discontinued the study due to any clinical adverse event was 9.5% in the placebo group and 8.9% in the FOSAMAX group. Adverse reactions from these studies considered by the investigators as possibly, probably, or definitely drug related in greater than or equal to 1% of patients treated with either FOSAMAX or placebo are presented in Table 1.

Table 1: Osteoporosis Treatment Studies in Postmenopausal Women Adverse Reactions Considered Possibly, Probably, or Definitely Drug Related by the Investigators and Reported in Greater Than or Equal to 1% of Patients
 | United States/Multinational Studies |  | Fracture Intervention Trial
 | FOSAMAX [10 mg/day for three years] % (n=196) | Placebo % (n=397) | FOSAMAX [5 mg/day for 2 years and 10 mg/day for either 1 or 2 additional years] % (n=3236) | Placebo % (n=3223)
Gastrointestinal
abdominal pain | 6.6 | 4.8 | 1.5 | 1.5
nausea | 3.6 | 4.0 | 1.1 | 1.5
dyspepsia | 3.6 | 3.5 | 1.1 | 1.2
constipation | 3.1 | 1.8 | 0.0 | 0.2
diarrhea | 3.1 | 1.8 | 0.6 | 0.3
flatulence | 2.6 | 0.5 | 0.2 | 0.3
acid regurgitation | 2.0 | 4.3 | 1.1 | 0.9
esophageal ulcer | 1.5 | 0.0 | 0.1 | 0.1
vomiting | 1.0 | 1.5 | 0.2 | 0.3
dysphagia | 1.0 | 0.0 | 0.1 | 0.1
abdominal distention | 1.0 | 0.8 | 0.0 | 0.0
gastritis | 0.5 | 1.3 | 0.6 | 0.7
Musculoskeletal
musculoskeletal (bone, muscle or joint) pain | 4.1 | 2.5 | 0.4 | 0.3
muscle cramp | 0.0 | 1.0 | 0.2 | 0.1
Nervous System/Psychiatric
headache | 2.6 | 1.5 | 0.2 | 0.2
dizziness | 0.0 | 1.0 | 0.0 | 0.1
Special Senses
taste perversion | 0.5 | 1.0 | 0.1 | 0.0

Rash and erythema have occurred.

Gastrointestinal Adverse Reactions: One patient treated with FOSAMAX (10 mg/day), who had a history of peptic ulcer disease and gastrectomy and who was taking concomitant aspirin, developed an anastomotic ulcer with mild hemorrhage, which was considered drug related. Aspirin and FOSAMAX were discontinued and the patient recovered. In the Study 1 and Study 2 populations, 49-54% had a history of gastrointestinal disorders at baseline and 54-89% used nonsteroidal anti-inflammatory drugs or aspirin at some time during the studies. [See Warnings and Precautions (5.1).]

Laboratory Test Findings: In double-blind, multicenter, controlled studies, asymptomatic, mild, and transient decreases in serum calcium and phosphate were observed in approximately 18% and 10%, respectively, of patients taking FOSAMAX versus approximately 12% and 3% of those taking placebo. However, the incidences of decreases in serum calcium to less than 8.0 mg/dL (2.0 mM) and serum phosphate to less than or equal to 2.0 mg/dL (0.65 mM) were similar in both treatment groups.

Weekly Dosing

The safety of FOSAMAX 70 mg once weekly for the treatment of postmenopausal osteoporosis was assessed in a one-year, double-blind, multicenter study comparing FOSAMAX 70 mg once weekly and FOSAMAX 10 mg daily. The overall safety and tolerability profiles of once weekly FOSAMAX 70 mg and FOSAMAX 10 mg daily were similar. The adverse reactions considered by the investigators as possibly, probably, or definitely drug related in greater than or equal to 1% of patients in either treatment group are presented in Table 2.

Table 2: Osteoporosis Treatment Studies in Postmenopausal Women Adverse Reactions Considered Possibly, Probably, or Definitely Drug Related by the Investigators and Reported in Greater Than or Equal to 1% of Patients
 | Once Weekly FOSAMAX 70 mg % (n=519) | FOSAMAX 10 mg/day % (n=370)
Gastrointestinal
abdominal pain | 3.7 | 3.0
dyspepsia | 2.7 | 2.2
acid regurgitation | 1.9 | 2.4
nausea | 1.9 | 2.4
abdominal distention | 1.0 | 1.4
constipation | 0.8 | 1.6
flatulence | 0.4 | 1.6
gastritis | 0.2 | 1.1
gastric ulcer | 0.0 | 1.1
Musculoskeletal
musculoskeletal (bone, muscle, joint) pain | 2.9 | 3.2
muscle cramp | 0.2 | 1.1

Prevention of Osteoporosis in Postmenopausal Women

Daily Dosing

The safety of FOSAMAX 5 mg/day in postmenopausal women 40-60 years of age has been evaluated in three double-blind, placebo-controlled studies involving over 1,400 patients randomized to receive FOSAMAX for either two or three years. In these studies the overall safety profiles of FOSAMAX 5 mg/day and placebo were similar. Discontinuation of therapy due to any clinical adverse event occurred in 7.5% of 642 patients treated with FOSAMAX 5 mg/day and 5.7% of 648 patients treated with placebo.

Weekly Dosing

The safety of FOSAMAX 35 mg once weekly compared to FOSAMAX 5 mg daily was evaluated in a one-year, double-blind, multicenter study of 723 patients. The overall safety and tolerability profiles of once weekly FOSAMAX 35 mg and FOSAMAX 5 mg daily were similar.

The adverse reactions from these studies considered by the investigators as possibly, probably, or definitely drug related in greater than or equal to 1% of patients treated with either once weekly FOSAMAX 35 mg, FOSAMAX 5 mg/day or placebo are presented in Table 3.

Table 3: Osteoporosis Prevention Studies in Postmenopausal Women Adverse Reactions Considered Possibly, Probably, or Definitely Drug Related by the Investigators and Reported in Greater Than or Equal to 1% of Patients
 | Two/Three-Year Studies |  | One-Year Study
 | FOSAMAX 5 mg/day % (n=642) | Placebo % (n=648) | FOSAMAX 5 mg/day % (n=361) | Once Weekly FOSAMAX 35 mg % (n=362)
Gastrointestinal
dyspepsia | 1.9 | 1.4 | 2.2 | 1.7
abdominal pain | 1.7 | 3.4 | 4.2 | 2.2
acid regurgitation | 1.4 | 2.5 | 4.2 | 4.7
nausea | 1.4 | 1.4 | 2.5 | 1.4
diarrhea | 1.1 | 1.7 | 1.1 | 0.6
constipation | 0.9 | 0.5 | 1.7 | 0.3
abdominal distention | 0.2 | 0.3 | 1.4 | 1.1
Musculoskeletal
musculoskeletal (bone, muscle or joint) pain | 0.8 | 0.9 | 1.9 | 2.2

Concomitant Use with Estrogen/Hormone Replacement Therapy

In two studies (of one and two years' duration) of postmenopausal osteoporotic women (total: n=853), the safety and tolerability profile of combined treatment with FOSAMAX 10 mg once daily and estrogen ± progestin (n=354) was consistent with those of the individual treatments.

Osteoporosis in Men

In two placebo-controlled, double-blind, multicenter studies in men (a two-year study of FOSAMAX 10 mg/day and a one-year study of once weekly FOSAMAX 70 mg) the rates of discontinuation of therapy due to any clinical adverse event were 2.7% for FOSAMAX 10 mg/day vs. 10.5% for placebo, and 6.4% for once weekly FOSAMAX 70 mg vs. 8.6% for placebo. The adverse reactions considered by the investigators as possibly, probably, or definitely drug related in greater than or equal to 2% of patients treated with either FOSAMAX or placebo are presented in Table 4.

Table 4: Osteoporosis Studies in Men Adverse Reactions Considered Possibly, Probably, or Definitely Drug Related by the Investigators and Reported in Greater Than or Equal to 2% of Patients
 | Two-year Study |  | One-year Study
 | FOSAMAX 10 mg/day % (n=146) | Placebo % (n=95) | Once Weekly FOSAMAX 70 mg % (n=109) | Placebo % (n=58)
Gastrointestinal
acid regurgitation | 4.1 | 3.2 | 0.0 | 0.0
flatulence | 4.1 | 1.1 | 0.0 | 0.0
gastroesophageal reflux disease | 0.7 | 3.2 | 2.8 | 0.0
dyspepsia | 3.4 | 0.0 | 2.8 | 1.7
diarrhea | 1.4 | 1.1 | 2.8 | 0.0
abdominal pain | 2.1 | 1.1 | 0.9 | 3.4
nausea | 2.1 | 0.0 | 0.0 | 0.0

Glucocorticoid-Induced Osteoporosis

In two, one-year, placebo-controlled, double-blind, multicenter studies in patients receiving glucocorticoid treatment, the overall safety and tolerability profiles of FOSAMAX 5 and 10 mg/day were generally similar to that of placebo. The adverse reactions considered by the investigators as possibly, probably, or definitely drug related in greater than or equal to 1% of patients treated with either FOSAMAX 5 or 10 mg/day or placebo are presented in Table 5.

Table 5: One-Year Studies in Glucocorticoid-Treated Patients Adverse Reactions Considered Possibly, Probably, or Definitely Drug Related by the Investigators and Reported in Greater Than or Equal to 1% of Patients
 | FOSAMAX 10 mg/day % (n=157) | FOSAMAX 5 mg/day % (n=161) | Placebo % (n=159)
Gastrointestinal
abdominal pain | 3.2 | 1.9 | 0.0
acid regurgitation | 2.5 | 1.9 | 1.3
constipation | 1.3 | 0.6 | 0.0
melena | 1.3 | 0.0 | 0.0
nausea | 0.6 | 1.2 | 0.6
diarrhea | 0.0 | 0.0 | 1.3
Nervous System/Psychiatric
headache | 0.6 | 0.0 | 1.3

The overall safety and tolerability profile in the glucocorticoid-induced osteoporosis population that continued therapy for the second year of the studies (FOSAMAX: n=147) was consistent with that observed in the first year.

Paget's Disease of Bone

In clinical studies (osteoporosis and Paget's disease), adverse events reported in 175 patients taking FOSAMAX 40 mg/day for 3-12 months were similar to those in postmenopausal women treated with FOSAMAX 10 mg/day. However, there was an apparent increased incidence of upper gastrointestinal adverse reactions in patients taking FOSAMAX 40 mg/day (17.7% FOSAMAX vs. 10.2% placebo). One case of esophagitis and two cases of gastritis resulted in discontinuation of treatment.

Additionally, musculoskeletal (bone, muscle or joint) pain, which has been described in patients with Paget's disease treated with other bisphosphonates, was considered by the investigators as possibly, probably, or definitely drug related in approximately 6% of patients treated with FOSAMAX 40 mg/day versus approximately 1% of patients treated with placebo, but rarely resulted in discontinuation of therapy. Discontinuation of therapy due to any clinical adverse events occurred in 6.4% of patients with Paget's disease treated with FOSAMAX 40 mg/day and 2.4% of patients treated with placebo.

6.2 Post-Marketing Experience

The following adverse reactions have been identified during post-approval use of FOSAMAX or bisphosphonate products. Because these reactions are reported voluntarily from a population of uncertain size, it is not always possible to reliably estimate their frequency or establish a causal relationship to drug exposure.

Body as a Whole: hypersensitivity reactions including urticaria and angioedema. Transient symptoms of myalgia, malaise, asthenia and fever have been reported with FOSAMAX, typically in association with initiation of treatment. Symptomatic hypocalcemia has occurred, generally in association with predisposing conditions. Peripheral edema.

Gastrointestinal: esophagitis, esophageal erosions, esophageal ulcers, esophageal stricture or perforation, and oropharyngeal ulceration. Gastric or duodenal ulcers, some severe and with complications, have also been reported [see Dosage and Administration (2.6); Warnings and Precautions (5.1)].

Localized osteonecrosis of the jaw, generally associated with tooth extraction and/or local infection with delayed healing, has been reported [see Warnings and Precautions (5.4)].

Musculoskeletal: bone, joint, and/or muscle pain, occasionally severe, and incapacitating [see Warnings and Precautions (5.3)]; joint swelling; low-energy femoral shaft and subtrochanteric fractures, and atypical fractures of other bones [see Warnings and Precautions (5.5)].

Nervous System: dizziness and vertigo.

Pulmonary: acute asthma exacerbations.

Skin: rash (occasionally with photosensitivity), pruritus, alopecia, severe skin reactions, including Stevens-Johnson syndrome and toxic epidermal necrolysis.

Special Senses: uveitis, scleritis or episcleritis. Cholesteatoma of the external auditory canal (focal osteonecrosis).

7 DRUG INTERACTIONS

7.1 Calcium Supplements/Antacids

Co-administration of FOSAMAX and calcium, antacids, or oral medications containing multivalent cations will interfere with absorption of FOSAMAX. Therefore, instruct patients to wait at least one-half hour after taking FOSAMAX before taking any other oral medications.

7.2 Aspirin

In clinical studies, the incidence of upper gastrointestinal adverse events was increased in patients receiving concomitant therapy with daily doses of FOSAMAX greater than 10 mg and aspirin-containing products.

7.3 Nonsteroidal Anti-Inflammatory Drugs

FOSAMAX may be administered to patients taking nonsteroidal anti-inflammatory drugs (NSAIDs). In a 3-year, controlled, clinical study (n=2027) during which a majority of patients received concomitant NSAIDs, the incidence of upper gastrointestinal adverse events was similar in patients taking FOSAMAX 5 or 10 mg/day compared to those taking placebo. However, since NSAID use is associated with gastrointestinal irritation, caution should be used during concomitant use with FOSAMAX.

8 USE IN SPECIFIC POPULATIONS

8.1 Pregnancy

Risk Summary

Available data on the use of FOSAMAX in pregnant women are insufficient to inform a drug-associated risk of adverse maternal or fetal outcomes. Discontinue FOSAMAX when pregnancy is recognized.

In animal reproduction studies, daily oral administration of alendronate to rats from before mating through the end of gestation or lactation showed decreased postimplantation survival and decreased pup body weight gain starting at doses equivalent to less than half of the highest recommended 40 mg clinical daily dose (based on body surface area, mg/m^2). Oral administration of alendronate to rats during organogenesis resulted in reduced fetal ossification starting at doses 3 times the 40 mg clinical daily dose. No similar fetal effects were observed in pregnant rabbits dosed orally during organogenesis at doses equivalent to approximately 10 times the 40 mg clinical daily dose.

Delayed or failed delivery of offspring, protracted parturition, and late pregnancy maternal and fetal deaths due to maternal hypocalcemia occurred in rats at oral doses as low as one tenth the 40 mg clinical daily dose (see Data).

Bisphosphonates are incorporated into the bone matrix, from which they are gradually released over a period of years. The amount of bisphosphonate incorporated into adult bone and available for release into the systemic circulation is directly related to the dose and duration of bisphosphonate use. Consequently, based on the mechanism of action of bisphosphonates, there is a potential risk of fetal harm, predominantly skeletal, if a woman becomes pregnant after completing a course of bisphosphonate therapy. The impact of variables such as time between cessation of bisphosphonate therapy to conception, the particular bisphosphonate used, and the route of administration (intravenous versus oral) on the risk has not been studied.

The estimated background risk of major birth defects and miscarriage for the indicated population(s) is unknown. All pregnancies have a background risk of birth defects, loss, or other adverse outcomes. In the U.S. general population, the estimated background risks of major birth defects and miscarriage in clinically recognized pregnancies is 2-4% and 15-20%, respectively.

Data

Animal Data

Reproduction studies in rats dosed orally from before mating to the end of gestation or lactation showed decreased postimplantation survival starting at 2 mg/kg/day and decreased body weight gain starting at 1 mg/kg/day, doses equivalent to less than half the 40 mg clinical daily dose based on body surface area, mg/m^2. Incidence of incomplete fetal ossification in vertebral, skull, and sternebral bones were increased in rats dosed orally during organogenesis starting at 10 mg/kg/day (approximately 3 times the 40 mg clinical daily dose). No similar fetal effects were observed in pregnant rabbits dosed orally during organogenesis at up to 35 mg/kg/day (equivalent to approximately 10 times the 40 mg clinical daily dose).

Both total and ionized calcium decreased in pregnant rats dosed orally with 15 mg/kg/day alendronate (approximately 4 times the 40 mg clinical daily dose) resulting in delays and failures of delivery. Protracted parturition due to maternal hypocalcemia was observed when rats were treated from before mating through gestation starting at 0.5 mg/kg/day (approximately one tenth the 40 mg clinical daily dose). Maternotoxicity (late pregnancy deaths) also occurred in female rats treated orally with 15 mg/kg/day (approximately 4 times the 40 mg clinical daily dose) for varying gestational time periods. These maternal deaths were lessened but not eliminated by cessation of treatment. Calcium supplementation in the drinking water or by subcutaneous minipump to rats dosed orally with 15 mg/kg/day alendronate could not ameliorate the hypocalcemia or prevent the dystocia-related maternal and neonatal deaths. However, intravenous calcium supplementation prevented maternal, but not neonatal deaths.

8.2 Lactation

Risk Summary

It is not known whether alendronate is present in human breast milk, affects human milk production, or has effects on the breastfed infant. The developmental and health benefits of breastfeeding should be considered along with the mother's clinical need for FOSAMAX and any potential adverse effects on the breastfed child from FOSAMAX or from the underlying maternal condition.

8.4 Pediatric Use

FOSAMAX is not indicated for use in pediatric patients.

The safety and efficacy of FOSAMAX were examined in a randomized, double-blind, placebo-controlled two-year study of 139 pediatric patients, aged 4-18 years, with severe osteogenesis imperfecta (OI). One-hundred-and-nine patients were randomized to 5 mg FOSAMAX daily (weight less than 40 kg) or 10 mg FOSAMAX daily (weight greater than or equal to 40 kg) and 30 patients to placebo. The mean baseline lumbar spine BMD Z-score of the patients was -4.5. The mean change in lumbar spine BMD Z-score from baseline to Month 24 was 1.3 in the FOSAMAX-treated patients and 0.1 in the placebo-treated patients. Treatment with FOSAMAX did not reduce the risk of fracture. Sixteen percent of the FOSAMAX patients who sustained a radiologically-confirmed fracture by Month 12 of the study had delayed fracture healing (callus remodeling) or fracture non-union when assessed radiographically at Month 24 compared with 9% of the placebo-treated patients. In FOSAMAX-treated patients, bone histomorphometry data obtained at Month 24 demonstrated decreased bone turnover and delayed mineralization time; however, there were no mineralization defects. There were no statistically significant differences between the FOSAMAX and placebo groups in reduction of bone pain. The oral bioavailability in children was similar to that observed in adults.

The overall safety profile of FOSAMAX in osteogenesis imperfecta patients treated for up to 24 months was generally similar to that of adults with osteoporosis treated with FOSAMAX. However, there was an increased occurrence of vomiting in osteogenesis imperfecta patients treated with FOSAMAX compared to placebo. During the 24-month treatment period, vomiting was observed in 32 of 109 (29.4%) patients treated with FOSAMAX and 3 of 30 (10%) patients treated with placebo.

In a pharmacokinetic study, 6 of 24 pediatric osteogenesis imperfecta patients who received a single oral dose of FOSAMAX 35 or 70 mg developed fever, flu-like symptoms, and/or mild lymphocytopenia within 24 to 48 hours after administration. These events, lasting no more than 2 to 3 days and responding to acetaminophen, are consistent with an acute-phase response that has been reported in patients receiving bisphosphonates, including FOSAMAX. [See Adverse Reactions (6.2).]

8.5 Geriatric Use

Of the patients receiving FOSAMAX in the Fracture Intervention Trial (FIT), 71% (n=2302) were greater than or equal to 65 years of age and 17% (n=550) were greater than or equal to 75 years of age. Of the patients receiving FOSAMAX in the United States and Multinational osteoporosis treatment studies in women, osteoporosis studies in men, glucocorticoid-induced osteoporosis studies, and Paget's disease studies [see Clinical Studies (14.1), (14.3), (14.4), (14.5)], 45%, 54%, 37%, and 70%, respectively, were 65 years of age or over. No overall differences in efficacy or safety were observed between these patients and younger patients, but greater sensitivity of some older individuals cannot be ruled out.

8.6 Renal Impairment

FOSAMAX is not recommended for patients with creatinine clearance less than 35 mL/min. No dosage adjustment is necessary in patients with creatinine clearance values between 35-60 mL/min [see Clinical Pharmacology (12.3)].

8.7 Hepatic Impairment

As there is evidence that alendronate is not metabolized or excreted in the bile, no studies were conducted in patients with hepatic impairment. No dosage adjustment is necessary [see Clinical Pharmacology (12.3)].

10 OVERDOSAGE

Significant lethality after single oral doses was seen in female rats and mice at 552 mg/kg (3256 mg/m^2) and 966 mg/kg (2898 mg/m^2), respectively. In males, these values were slightly higher, 626 and 1280 mg/kg, respectively. There was no lethality in dogs at oral doses up to 200 mg/kg (4000 mg/m^2).

No specific information is available on the treatment of overdosage with FOSAMAX. Hypocalcemia, hypophosphatemia, and upper gastrointestinal adverse events, such as upset stomach, heartburn, esophagitis, gastritis, or ulcer, may result from oral overdosage. Milk or antacids should be given to bind alendronate. Due to the risk of esophageal irritation, vomiting should not be induced and the patient should remain fully upright.

Dialysis would not be beneficial.

11 DESCRIPTION

FOSAMAX (alendronate sodium) is a bisphosphonate that acts as a specific inhibitor of osteoclast-mediated bone resorption. Bisphosphonates are synthetic analogs of pyrophosphate that bind to the hydroxyapatite found in bone.

Alendronate sodium is chemically described as (4-amino-1-hydroxybutylidene) bisphosphonic acid monosodium salt trihydrate.

The empirical formula of alendronate sodium is C4H12NNaO7P2•3H2O and its formula weight is 325.12. The structural formula is:

Alendronate sodium is a white, crystalline, nonhygroscopic powder. It is soluble in water, very slightly soluble in alcohol, and practically insoluble in chloroform.

FOSAMAX tablets for oral administration contain 91.37 mg of alendronate monosodium salt trihydrate, which is the molar equivalent of 70 mg of free acid, and the following inactive ingredients: microcrystalline cellulose, anhydrous lactose, croscarmellose sodium, and magnesium stearate.

12 CLINICAL PHARMACOLOGY

12.1 Mechanism of Action

Animal studies have indicated the following mode of action. At the cellular level, alendronate shows preferential localization to sites of bone resorption, specifically under osteoclasts. The osteoclasts adhere normally to the bone surface but lack the ruffled border that is indicative of active resorption. Alendronate does not interfere with osteoclast recruitment or attachment, but it does inhibit osteoclast activity. Studies in mice on the localization of radioactive [^3H]alendronate in bone showed about 10-fold higher uptake on osteoclast surfaces than on osteoblast surfaces. Bones examined 6 and 49 days after [^3H]alendronate administration in rats and mice, respectively, showed that normal bone was formed on top of the alendronate, which was incorporated inside the matrix. While incorporated in bone matrix, alendronate is not pharmacologically active. Thus, alendronate must be continuously administered to suppress osteoclasts on newly formed resorption surfaces. Histomorphometry in baboons and rats showed that alendronate treatment reduces bone turnover (i.e., the number of sites at which bone is remodeled). In addition, bone formation exceeds bone resorption at these remodeling sites, leading to progressive gains in bone mass.

12.2 Pharmacodynamics

Alendronate is a bisphosphonate that binds to bone hydroxyapatite and specifically inhibits the activity of osteoclasts, the bone-resorbing cells. Alendronate reduces bone resorption with no direct effect on bone formation, although the latter process is ultimately reduced because bone resorption and formation are coupled during bone turnover.

Osteoporosis in Postmenopausal Women

Osteoporosis is characterized by low bone mass that leads to an increased risk of fracture. The diagnosis can be confirmed by the finding of low bone mass, evidence of fracture on X-ray, a history of osteoporotic fracture, or height loss or kyphosis, indicative of vertebral (spinal) fracture. Osteoporosis occurs in both males and females but is most common among women following the menopause, when bone turnover increases and the rate of bone resorption exceeds that of bone formation. These changes result in progressive bone loss and lead to osteoporosis in a significant proportion of women over age 50. Fractures, usually of the spine, hip, and wrist, are the common consequences. From age 50 to age 90, the risk of hip fracture in white women increases 50-fold and the risk of vertebral fracture 15- to 30-fold. It is estimated that approximately 40% of 50-year-old women will sustain one or more osteoporosis-related fractures of the spine, hip, or wrist during their remaining lifetimes. Hip fractures, in particular, are associated with substantial morbidity, disability, and mortality.

Daily oral doses of alendronate (5, 20, and 40 mg for six weeks) in postmenopausal women produced biochemical changes indicative of dose-dependent inhibition of bone resorption, including decreases in urinary calcium and urinary markers of bone collagen degradation (such as deoxypyridinoline and cross-linked N-telopeptides of type I collagen). These biochemical changes tended to return toward baseline values as early as 3 weeks following the discontinuation of therapy with alendronate and did not differ from placebo after 7 months.

Long-term treatment of osteoporosis with FOSAMAX 10 mg/day (for up to five years) reduced urinary excretion of markers of bone resorption, deoxypyridinoline and cross-linked N-telopeptides of type l collagen, by approximately 50% and 70%, respectively, to reach levels similar to those seen in healthy premenopausal women. Similar decreases were seen in patients in osteoporosis prevention studies who received FOSAMAX 5 mg/day. The decrease in the rate of bone resorption indicated by these markers was evident as early as one month and at three to six months reached a plateau that was maintained for the entire duration of treatment with FOSAMAX. In osteoporosis treatment studies FOSAMAX 10 mg/day decreased the markers of bone formation, osteocalcin and bone specific alkaline phosphatase by approximately 50%, and total serum alkaline phosphatase by approximately 25 to 30% to reach a plateau after 6 to 12 months. In osteoporosis prevention studies FOSAMAX 5 mg/day decreased osteocalcin and total serum alkaline phosphatase by approximately 40% and 15%, respectively. Similar reductions in the rate of bone turnover were observed in postmenopausal women during one-year studies with once weekly FOSAMAX 70 mg for the treatment of osteoporosis and once weekly FOSAMAX 35 mg for the prevention of osteoporosis. These data indicate that the rate of bone turnover reached a new steady-state, despite the progressive increase in the total amount of alendronate deposited within bone.

As a result of inhibition of bone resorption, asymptomatic reductions in serum calcium and phosphate concentrations were also observed following treatment with FOSAMAX. In the long-term studies, reductions from baseline in serum calcium (approximately 2%) and phosphate (approximately 4 to 6%) were evident the first month after the initiation of FOSAMAX 10 mg. No further decreases in serum calcium were observed for the five-year duration of treatment; however, serum phosphate returned toward prestudy levels during years three through five. Similar reductions were observed with FOSAMAX 5 mg/day. In one-year studies with once weekly FOSAMAX 35 and 70 mg, similar reductions were observed at 6 and 12 months. The reduction in serum phosphate may reflect not only the positive bone mineral balance due to FOSAMAX but also a decrease in renal phosphate reabsorption.

Osteoporosis in Men

Treatment of men with osteoporosis with FOSAMAX 10 mg/day for two years reduced urinary excretion of cross-linked N-telopeptides of type I collagen by approximately 60% and bone-specific alkaline phosphatase by approximately 40%. Similar reductions were observed in a one-year study in men with osteoporosis receiving once weekly FOSAMAX 70 mg.

Glucocorticoid-Induced Osteoporosis

Sustained use of glucocorticoids is commonly associated with development of osteoporosis and resulting fractures (especially vertebral, hip, and rib). It occurs both in males and females of all ages. Osteoporosis occurs as a result of inhibited bone formation and increased bone resorption resulting in net bone loss. Alendronate decreases bone resorption without directly inhibiting bone formation.

In clinical studies of up to two years' duration, FOSAMAX 5 and 10 mg/day reduced cross-linked N-telopeptides of type I collagen (a marker of bone resorption) by approximately 60% and reduced bone-specific alkaline phosphatase and total serum alkaline phosphatase (markers of bone formation) by approximately 15 to 30% and 8 to 18%, respectively. As a result of inhibition of bone resorption, FOSAMAX 5 and 10 mg/day induced asymptomatic decreases in serum calcium (approximately 1 to 2%) and serum phosphate (approximately 1 to 8%).

Paget's Disease of Bone

Paget's disease of bone is a chronic, focal skeletal disorder characterized by greatly increased and disorderly bone remodeling. Excessive osteoclastic bone resorption is followed by osteoblastic new bone formation, leading to the replacement of the normal bone architecture by disorganized, enlarged, and weakened bone structure.

Clinical manifestations of Paget's disease range from no symptoms to severe morbidity due to bone pain, bone deformity, pathological fractures, and neurological and other complications. Serum alkaline phosphatase, the most frequently used biochemical index of disease activity, provides an objective measure of disease severity and response to therapy.

FOSAMAX decreases the rate of bone resorption directly, which leads to an indirect decrease in bone formation. In clinical trials, FOSAMAX 40 mg once daily for six months produced significant decreases in serum alkaline phosphatase as well as in urinary markers of bone collagen degradation. As a result of the inhibition of bone resorption, FOSAMAX induced generally mild, transient, and asymptomatic decreases in serum calcium and phosphate.

12.3 Pharmacokinetics

Absorption

Relative to an intravenous reference dose, the mean oral bioavailability of alendronate in women was 0.64% for doses ranging from 5 to 70 mg when administered after an overnight fast and two hours before a standardized breakfast. Oral bioavailability of the 10 mg tablet in men (0.59%) was similar to that in women when administered after an overnight fast and 2 hours before breakfast.

FOSAMAX 70 mg oral solution and FOSAMAX 70 mg tablet are equally bioavailable.

A study examining the effect of timing of a meal on the bioavailability of alendronate was performed in 49 postmenopausal women. Bioavailability was decreased (by approximately 40%) when 10 mg alendronate was administered either 0.5 or 1 hour before a standardized breakfast, when compared to dosing 2 hours before eating. In studies of treatment and prevention of osteoporosis, alendronate was effective when administered at least 30 minutes before breakfast.

Bioavailability was negligible whether alendronate was administered with or up to two hours after a standardized breakfast. Concomitant administration of alendronate with coffee or orange juice reduced bioavailability by approximately 60%.

Distribution

Preclinical studies (in male rats) show that alendronate transiently distributes to soft tissues following 1 mg/kg intravenous administration but is then rapidly redistributed to bone or excreted in the urine. The mean steady-state volume of distribution, exclusive of bone, is at least 28 L in humans. Concentrations of drug in plasma following therapeutic oral doses are too low (less than 5 ng/mL) for analytical detection. Protein binding in human plasma is approximately 78%.

Metabolism

There is no evidence that alendronate is metabolized in animals or humans.

Excretion

Following a single intravenous dose of [^14C]alendronate, approximately 50% of the radioactivity was excreted in the urine within 72 hours and little or no radioactivity was recovered in the feces. Following a single 10 mg intravenous dose, the renal clearance of alendronate was 71 mL/min (64, 78; 90% confidence interval [CI]), and systemic clearance did not exceed 200 mL/min. Plasma concentrations fell by more than 95% within 6 hours following intravenous administration. The terminal half-life in humans is estimated to exceed 10 years, probably reflecting release of alendronate from the skeleton. Based on the above, it is estimated that after 10 years of oral treatment with FOSAMAX (10 mg daily) the amount of alendronate released daily from the skeleton is approximately 25% of that absorbed from the gastrointestinal tract.

Specific Populations

Gender: Bioavailability and the fraction of an intravenous dose excreted in urine were similar in men and women.

Geriatric: Bioavailability and disposition (urinary excretion) were similar in elderly and younger patients. No dosage adjustment is necessary in elderly patients.

Race: Pharmacokinetic differences due to race have not been studied.

Renal Impairment: Preclinical studies show that, in rats with kidney failure, increasing amounts of drug are present in plasma, kidney, spleen, and tibia. In healthy controls, drug that is not deposited in bone is rapidly excreted in the urine. No evidence of saturation of bone uptake was found after 3 weeks dosing with cumulative intravenous doses of 35 mg/kg in young male rats. Although no formal renal impairment pharmacokinetic study has been conducted in patients, it is likely that, as in animals, elimination of alendronate via the kidney will be reduced in patients with impaired renal function. Therefore, somewhat greater accumulation of alendronate in bone might be expected in patients with impaired renal function.

No dosage adjustment is necessary for patients with creatinine clearance 35 to 60 mL/min. FOSAMAX is not recommended for patients with creatinine clearance less than 35 mL/min due to lack of experience with alendronate in renal failure.

Hepatic Impairment: As there is evidence that alendronate is not metabolized or excreted in the bile, no studies were conducted in patients with hepatic impairment. No dosage adjustment is necessary.

Drug Interactions

Intravenous ranitidine was shown to double the bioavailability of oral alendronate. The clinical significance of this increased bioavailability and whether similar increases will occur in patients given oral H2-antagonists is unknown.

In healthy subjects, oral prednisone (20 mg three times daily for five days) did not produce a clinically meaningful change in the oral bioavailability of alendronate (a mean increase ranging from 20 to 44%).

Products containing calcium and other multivalent cations are likely to interfere with absorption of alendronate.

13 NONCLINICAL TOXICOLOGY

13.1 Carcinogenesis, Mutagenesis, Impairment of Fertility

Harderian gland (a retro-orbital gland not present in humans) adenomas were increased in high-dose female mice (p=0.003) in a 92-week oral carcinogenicity study at doses of alendronate of 1, 3, and 10 mg/kg/day (males) or 1, 2, and 5 mg/kg/day (females). These doses are equivalent to approximately 0.1 to 1 times the highest recommended clinical daily dose of 40 mg based on surface area, mg/m^2. The relevance of this finding to humans is unknown.

Parafollicular cell (thyroid) adenomas were increased in high-dose male rats (p=0.003) in a 2-year oral carcinogenicity study at doses of 1 and 3.75 mg/kg body weight. These doses are equivalent to approximately 0.3 and 1 times the 40 mg clinical daily dose based on surface area, mg/m^2. The relevance of this finding to humans is unknown.

Alendronate was not genotoxic in the in vitro microbial mutagenesis assay with and without metabolic activation, in an in vitro mammalian cell mutagenesis assay, in an in vitro alkaline elution assay in rat hepatocytes, and in an in vivo chromosomal aberration assay in mice. In an in vitro chromosomal aberration assay in Chinese hamster ovary cells, however, alendronate gave equivocal results.

Alendronate had no effect on fertility (male or female) in rats at oral doses up to 5 mg/kg/day (approximately 1 times the 40 mg clinical daily dose based on surface area, mg/m^2).

13.2 Animal Toxicology and/or Pharmacology

The relative inhibitory activities on bone resorption and mineralization of alendronate and etidronate were compared in the Schenk assay, which is based on histological examination of the epiphyses of growing rats. In this assay, the lowest dose of alendronate that interfered with bone mineralization (leading to osteomalacia) was 6000-fold the antiresorptive dose. The corresponding ratio for etidronate was one to one. These data suggest that alendronate administered in therapeutic doses is highly unlikely to induce osteomalacia.

14 CLINICAL STUDIES

14.1 Treatment of Osteoporosis in Postmenopausal Women

Daily Dosing

The efficacy of FOSAMAX 10 mg daily was assessed in four clinical trials. Study 1, a three-year, multicenter, double-blind, placebo-controlled, US clinical study enrolled 478 patients with a BMD T-score at or below minus 2.5 with or without a prior vertebral fracture; Study 2, a three-year, multicenter, double-blind, placebo-controlled Multinational clinical study enrolled 516 patients with a BMD T-score at or below minus 2.5 with or without a prior vertebral fracture; Study 3, the Three-Year Study of the Fracture Intervention Trial (FIT) a study which enrolled 2027 postmenopausal patients with at least one baseline vertebral fracture; and Study 4, the Four-Year Study of FIT: a study which enrolled 4432 postmenopausal patients with low bone mass but without a baseline vertebral fracture.

Effect on Fracture Incidence

To assess the effects of FOSAMAX on the incidence of vertebral fractures (detected by digitized radiography; approximately one third of these were clinically symptomatic), the U.S. and Multinational studies were combined in an analysis that compared placebo to the pooled dosage groups of FOSAMAX (5 or 10 mg for three years or 20 mg for two years followed by 5 mg for one year). There was a statistically significant reduction in the proportion of patients treated with FOSAMAX experiencing one or more new vertebral fractures relative to those treated with placebo (3.2% vs. 6.2%; a 48% relative risk reduction). A reduction in the total number of new vertebral fractures (4.2 vs. 11.3 per 100 patients) was also observed. In the pooled analysis, patients who received FOSAMAX had a loss in stature that was statistically significantly less than was observed in those who received placebo (-3.0 mm vs. -4.6 mm).

The Fracture Intervention Trial (FIT) consisted of two studies in postmenopausal women: the Three-Year Study of patients who had at least one baseline radiographic vertebral fracture and the Four-Year Study of patients with low bone mass but without a baseline vertebral fracture. In both studies of FIT, 96% of randomized patients completed the studies (i.e., had a closeout visit at the scheduled end of the study); approximately 80% of patients were still taking study medication upon completion.

Fracture Intervention Trial: Three-Year Study (patients with at least one baseline radiographic vertebral fracture)

This randomized, double-blind, placebo-controlled, 2027-patient study (FOSAMAX, n=1022; placebo, n=1005) demonstrated that treatment with FOSAMAX resulted in statistically significant reductions in fracture incidence at three years as shown in Table 6.

Table 6: Effect of FOSAMAX on Fracture Incidence in the Three-Year Study of FIT (patients with vertebral fracture at baseline)
 | Percent of Patients
 | FOSAMAX (n=1022) | Placebo (n=1005) | Absolute Reduction in Fracture Incidence | Relative Reduction in Fracture Risk %
Patients with:
Vertebral fractures (diagnosed by X-ray) [Number evaluable for vertebral fractures: FOSAMAX, n=984; placebo, n=966]
≥1 new vertebral fracture | 7.9 | 15.0 | 7.1 | 47 [p<0.001,]
≥2 new vertebral fractures | 0.5 | 4.9 | 4.4 | 90
Clinical (symptomatic) fractures
Any clinical (symptomatic) fracture | 13.8 | 18.1 | 4.3 | 26 [p=0.007,]
≥1 clinical (symptomatic) vertebral fracture | 2.3 | 5.0 | 2.7 | 54 [p<0.01,]
Hip fracture | 1.1 | 2.2 | 1.1 | 51 [p<0.05]
Wrist (forearm) fracture | 2.2 | 4.1 | 1.9 | 48

Furthermore, in this population of patients with baseline vertebral fracture, treatment with FOSAMAX significantly reduced the incidence of hospitalizations (25.0% vs. 30.7%).

In the Three-Year Study of FIT, fractures of the hip occurred in 22 (2.2%) of 1005 patients on placebo and 11 (1.1%) of 1022 patients on FOSAMAX, p=0.047. Figure 1 displays the cumulative incidence of hip fractures in this study.

Figure 1:

Fracture Intervention Trial: Four-Year Study (patients with low bone mass but without a baseline radiographic vertebral fracture)

This randomized, double-blind, placebo-controlled, 4432-patient study (FOSAMAX, n=2214; placebo, n=2218) further investigated the reduction in fracture incidence due to FOSAMAX. The intent of the study was to recruit women with osteoporosis, defined as a baseline femoral neck BMD at least two standard deviations below the mean for young adult women. However, due to subsequent revisions to the normative values for femoral neck BMD, 31% of patients were found not to meet this entry criterion and thus this study included both osteoporotic and non-osteoporotic women. The results are shown in Table 7 for the patients with osteoporosis.

Table 7: Effect of FOSAMAX on Fracture Incidence in Osteoporotic [Baseline femoral neck BMD at least 2 SD below the mean for young adult women] Patients in the Four-Year Study of FIT (patients without vertebral fracture at baseline)
 | Percent of Patients
 | FOSAMAX (n=1545) | Placebo (n=1521) | Absolute Reduction in Fracture Incidence | Relative Reduction in Fracture Risk (%)
Patients with:
Vertebral fractures (diagnosed by X-ray) [Number evaluable for vertebral fractures: FOSAMAX, n=1426; placebo, n=1428]
≥1 new vertebral fracture | 2.5 | 4.8 | 2.3 | 48 [p<0.001,]
≥2 new vertebral fractures | 0.1 | 0.6 | 0.5 | 78 [p=0.035,]
Clinical (symptomatic) fractures
Any clinical (symptomatic) fracture | 12.9 | 16.2 | 3.3 | 22 [p=0.01]
≥1 clinical (symptomatic) vertebral fracture | 1.0 | 1.6 | 0.6 | 41 (NS) [Not significant. This study was not powered to detect differences at these sites.]
Hip fracture | 1.0 | 1.4 | 0.4 | 29 (NS)
Wrist (forearm) fracture | 3.9 | 3.8 | -0.1 | NS

Fracture Results Across Studies

In the Three-Year Study of FIT, FOSAMAX reduced the percentage of women experiencing at least one new radiographic vertebral fracture from 15.0% to 7.9% (47% relative risk reduction, p<0.001); in the Four-Year Study of FIT, the percentage was reduced from 3.8% to 2.1% (44% relative risk reduction, p=0.001); and in the combined U.S./Multinational studies, from 6.2% to 3.2% (48% relative risk reduction, p=0.034).

FOSAMAX reduced the percentage of women experiencing multiple (two or more) new vertebral fractures from 4.2% to 0.6% (87% relative risk reduction, p<0.001) in the combined U.S./Multinational studies and from 4.9% to 0.5% (90% relative risk reduction, p<0.001) in the Three-Year Study of FIT. In the Four-Year Study of FIT, FOSAMAX reduced the percentage of osteoporotic women experiencing multiple vertebral fractures from 0.6% to 0.1% (78% relative risk reduction, p=0.035).

Thus, FOSAMAX reduced the incidence of radiographic vertebral fractures in osteoporotic women whether or not they had a previous radiographic vertebral fracture.

Effect on Bone Mineral Density

The bone mineral density efficacy of FOSAMAX 10 mg once daily in postmenopausal women, 44 to 84 years of age, with osteoporosis (lumbar spine bone mineral density [BMD] of at least 2 standard deviations below the premenopausal mean) was demonstrated in four double-blind, placebo-controlled clinical studies of two or three years' duration.

Figure 2 shows the mean increases in BMD of the lumbar spine, femoral neck, and trochanter in patients receiving FOSAMAX 10 mg/day relative to placebo-treated patients at three years for each of these studies.

Figure 2:

At three years significant increases in BMD, relative both to baseline and placebo, were seen at each measurement site in each study in patients who received FOSAMAX 10 mg/day. Total body BMD also increased significantly in each study, suggesting that the increases in bone mass of the spine and hip did not occur at the expense of other skeletal sites. Increases in BMD were evident as early as three months and continued throughout the three years of treatment. (See Figure 3 for lumbar spine results.) In the two-year extension of these studies, treatment of 147 patients with FOSAMAX 10 mg/day resulted in continued increases in BMD at the lumbar spine and trochanter (absolute additional increases between years 3 and 5: lumbar spine, 0.94%; trochanter, 0.88%). BMD at the femoral neck, forearm and total body were maintained. FOSAMAX was similarly effective regardless of age, race, baseline rate of bone turnover, and baseline BMD in the range studied (at least 2 standard deviations below the premenopausal mean).

Figure 3:

In patients with postmenopausal osteoporosis treated with FOSAMAX 10 mg/day for one or two years, the effects of treatment withdrawal were assessed. Following discontinuation, there were no further increases in bone mass and the rates of bone loss were similar to those of the placebo groups.

Bone Histology

Bone histology in 270 postmenopausal patients with osteoporosis treated with FOSAMAX at doses ranging from 1 to 20 mg/day for one, two, or three years revealed normal mineralization and structure, as well as the expected decrease in bone turnover relative to placebo. These data, together with the normal bone histology and increased bone strength observed in rats and baboons exposed to long-term alendronate treatment, support the conclusion that bone formed during therapy with FOSAMAX is of normal quality.

Effect on Height

FOSAMAX, over a three- or four-year period, was associated with statistically significant reductions in loss of height vs. placebo in patients with and without baseline radiographic vertebral fractures. At the end of the FIT studies, the between-treatment group differences were 3.2 mm in the Three-Year Study and 1.3 mm in the Four-Year Study.

Weekly Dosing

The therapeutic equivalence of once-weekly FOSAMAX 70 mg (n=519) and FOSAMAX 10 mg daily (n=370) was demonstrated in a one-year, double-blind, multicenter study of postmenopausal women with osteoporosis. In the primary analysis of completers, the mean increases from baseline in lumbar spine BMD at one year were 5.1% (4.8, 5.4%; 95% CI) in the 70-mg once-weekly group (n=440) and 5.4% (5.0, 5.8%; 95% CI) in the 10-mg daily group (n=330). The two treatment groups were also similar with regard to BMD increases at other skeletal sites. The results of the intention-to-treat analysis were consistent with the primary analysis of completers.

Concomitant Use with Estrogen/Hormone Replacement Therapy (HRT)

The effects on BMD of treatment with FOSAMAX 10 mg once daily and conjugated estrogen (0.625 mg/day) either alone or in combination were assessed in a two-year, double-blind, placebo-controlled study of hysterectomized postmenopausal osteoporotic women (n=425). At two years, the increases in lumbar spine BMD from baseline were significantly greater with the combination (8.3%) than with either estrogen or FOSAMAX alone (both 6.0%).

The effects on BMD when FOSAMAX was added to stable doses (for at least one year) of HRT (estrogen ± progestin) were assessed in a one-year, double-blind, placebo-controlled study in postmenopausal osteoporotic women (n=428). The addition of FOSAMAX 10 mg once daily to HRT produced, at one year, significantly greater increases in lumbar spine BMD (3.7%) vs. HRT alone (1.1%).

In these studies, significant increases or favorable trends in BMD for combined therapy compared with HRT alone were seen at the total hip, femoral neck, and trochanter. No significant effect was seen for total body BMD.

Histomorphometric studies of transiliac biopsies in 92 subjects showed normal bone architecture. Compared to placebo there was a 98% suppression of bone turnover (as assessed by mineralizing surface) after 18 months of combined treatment with FOSAMAX and HRT, 94% on FOSAMAX alone, and 78% on HRT alone. The long-term effects of combined FOSAMAX and HRT on fracture occurrence and fracture healing have not been studied.

14.2 Prevention of Osteoporosis in Postmenopausal Women

Daily Dosing

Prevention of bone loss was demonstrated in two double-blind, placebo-controlled studies of postmenopausal women 40-60 years of age. One thousand six hundred nine patients (FOSAMAX 5 mg/day; n=498) who were at least six months postmenopausal were entered into a two-year study without regard to their baseline BMD. In the other study, 447 patients (FOSAMAX 5 mg/day; n=88), who were between six months and three years postmenopause, were treated for up to three years. In the placebo-treated patients BMD losses of approximately 1% per year were seen at the spine, hip (femoral neck and trochanter) and total body. In contrast, FOSAMAX 5 mg/day prevented bone loss in the majority of patients and induced significant increases in mean bone mass at each of these sites (see Figure 4). In addition, FOSAMAX 5 mg/day reduced the rate of bone loss at the forearm by approximately half relative to placebo. FOSAMAX 5 mg/day was similarly effective in this population regardless of age, time since menopause, race and baseline rate of bone turnover.

Figure 4:

Bone Histology

Bone histology was normal in the 28 patients biopsied at the end of three years who received FOSAMAX at doses of up to 10 mg/day.

Weekly Dosing

The therapeutic equivalence of once weekly FOSAMAX 35 mg (n=362) and FOSAMAX 5 mg daily (n=361) was demonstrated in a one-year, double-blind, multicenter study of postmenopausal women without osteoporosis. In the primary analysis of completers, the mean increases from baseline in lumbar spine BMD at one year were 2.9% (2.6, 3.2%; 95% CI) in the 35-mg once-weekly group (n=307) and 3.2% (2.9, 3.5%; 95% CI) in the 5-mg daily group (n=298). The two treatment groups were also similar with regard to BMD increases at other skeletal sites. The results of the intention-to-treat analysis were consistent with the primary analysis of completers.

14.3 Treatment to Increase Bone Mass in Men with Osteoporosis

The efficacy of FOSAMAX in men with hypogonadal or idiopathic osteoporosis was demonstrated in two clinical studies.

Daily Dosing

A two-year, double-blind, placebo-controlled, multicenter study of FOSAMAX 10 mg once daily enrolled a total of 241 men between the ages of 31 and 87 (mean, 63). All patients in the trial had either a BMD T-score less than or equal to -2 at the femoral neck and less than or equal to -1 at the lumbar spine, or a baseline osteoporotic fracture and a BMD T-score less than or equal to -1 at the femoral neck. At two years, the mean increases relative to placebo in BMD in men receiving FOSAMAX 10 mg/day were significant at the following sites: lumbar spine, 5.3%; femoral neck, 2.6%; trochanter, 3.1%; and total body, 1.6%. Treatment with FOSAMAX also reduced height loss (FOSAMAX, -0.6 mm vs. placebo, -2.4 mm).

Weekly Dosing

A one-year, double-blind, placebo-controlled, multicenter study of once weekly FOSAMAX 70 mg enrolled a total of 167 men between the ages of 38 and 91 (mean, 66). Patients in the study had either a BMD T-score less than or equal to -2 at the femoral neck and less than or equal to -1 at the lumbar spine, or a BMD T-score less than or equal to -2 at the lumbar spine and less than or equal to -1 at the femoral neck, or a baseline osteoporotic fracture and a BMD T-score less than or equal to -1 at the femoral neck. At one year, the mean increases relative to placebo in BMD in men receiving FOSAMAX 70 mg once weekly were significant at the following sites: lumbar spine, 2.8%; femoral neck, 1.9%; trochanter, 2.0%; and total body, 1.2%. These increases in BMD were similar to those seen at one year in the 10 mg once-daily study.

In both studies, BMD responses were similar regardless of age (greater than or equal to 65 years vs. less than 65 years), gonadal function (baseline testosterone less than 9 ng/dL vs. greater than or equal to 9 ng/dL), or baseline BMD (femoral neck and lumbar spine T-score less than or equal to -2.5 vs. greater than -2.5).

14.4 Treatment of Glucocorticoid-Induced Osteoporosis

The efficacy of FOSAMAX 5 and 10 mg once daily in men and women receiving glucocorticoids (at least 7.5 mg/day of prednisone or equivalent) was demonstrated in two, one-year, double-blind, randomized, placebo-controlled, multicenter studies of virtually identical design, one performed in the United States and the other in 15 different countries (Multinational [which also included FOSAMAX 2.5 mg/day]). These studies enrolled 232 and 328 patients, respectively, between the ages of 17 and 83 with a variety of glucocorticoid-requiring diseases. Patients received supplemental calcium and vitamin D. Figure 5 shows the mean increases relative to placebo in BMD of the lumbar spine, femoral neck, and trochanter in patients receiving FOSAMAX 5 mg/day for each study.

Figure 5:

After one year, significant increases relative to placebo in BMD were seen in the combined studies at each of these sites in patients who received FOSAMAX 5 mg/day. In the placebo-treated patients, a significant decrease in BMD occurred at the femoral neck (-1.2%), and smaller decreases were seen at the lumbar spine and trochanter. Total body BMD was maintained with FOSAMAX 5 mg/day. The increases in BMD with FOSAMAX 10 mg/day were similar to those with FOSAMAX 5 mg/day in all patients except for postmenopausal women not receiving estrogen therapy. In these women, the increases (relative to placebo) with FOSAMAX 10 mg/day were greater than those with FOSAMAX 5 mg/day at the lumbar spine (4.1% vs. 1.6%) and trochanter (2.8% vs. 1.7%), but not at other sites. FOSAMAX was effective regardless of dose or duration of glucocorticoid use. In addition, FOSAMAX was similarly effective regardless of age (less than 65 vs. greater than or equal to 65 years), race (Caucasian vs. other races), gender, underlying disease, baseline BMD, baseline bone turnover, and use with a variety of common medications.

Bone histology was normal in the 49 patients biopsied at the end of one year who received FOSAMAX at doses of up to 10 mg/day.

Of the original 560 patients in these studies, 208 patients who remained on at least 7.5 mg/day of prednisone or equivalent continued into a one-year double-blind extension. After two years of treatment, spine BMD increased by 3.7% and 5.0% relative to placebo with FOSAMAX 5 and 10 mg/day, respectively. Significant increases in BMD (relative to placebo) were also observed at the femoral neck, trochanter, and total body.

After one year, 2.3% of patients treated with FOSAMAX 5 or 10 mg/day (pooled) vs. 3.7% of those treated with placebo experienced a new vertebral fracture (not significant). However, in the population studied for two years, treatment with FOSAMAX (pooled dosage groups: 5 or 10 mg for two years or 2.5 mg for one year followed by 10 mg for one year) significantly reduced the incidence of patients with a new vertebral fracture (FOSAMAX 0.7% vs. placebo 6.8%).

14.5 Treatment of Paget's Disease of Bone

The efficacy of FOSAMAX 40 mg once daily for six months was demonstrated in two double-blind clinical studies of male and female patients with moderate to severe Paget's disease (alkaline phosphatase at least twice the upper limit of normal): a placebo-controlled, multinational study and a U.S. comparative study with etidronate disodium 400 mg/day. Figure 6 shows the mean percent changes from baseline in serum alkaline phosphatase for up to six months of randomized treatment.

Figure 6:

At six months the suppression in alkaline phosphatase in patients treated with FOSAMAX was significantly greater than that achieved with etidronate and contrasted with the complete lack of response in placebo-treated patients. Response (defined as either normalization of serum alkaline phosphatase or decrease from baseline greater than or equal to 60%) occurred in approximately 85% of patients treated with FOSAMAX in the combined studies vs. 30% in the etidronate group and 0% in the placebo group. FOSAMAX was similarly effective regardless of age, gender, race, prior use of other bisphosphonates, or baseline alkaline phosphatase within the range studied (at least twice the upper limit of normal).

Bone histology was evaluated in 33 patients with Paget's disease treated with FOSAMAX 40 mg/day for 6 months. As in patients treated for osteoporosis [see Clinical Studies (14.1)], FOSAMAX did not impair mineralization, and the expected decrease in the rate of bone turnover was observed. Normal lamellar bone was produced during treatment with FOSAMAX, even where preexisting bone was woven and disorganized. Overall, bone histology data support the conclusion that bone formed during treatment with FOSAMAX is of normal quality.

16 HOW SUPPLIED/STORAGE AND HANDLING

How Supplied

FOSAMAX Tablets, 70 mg, are white, oval, uncoated tablets with code 31 on one side and an outline of a bone image on the other:

- NDC 78206-135-01 unit-of-use blister package of 4.

Storage

FOSAMAX Tablets:

Store in a well-closed container at room temperature, 59°F to 86°F (15°C to 30°C).

17 PATIENT COUNSELING INFORMATION

Advise the patient to read the FDA-approved patient labeling (Medication Guide).

Instruct patients to read the Medication Guide before starting therapy with FOSAMAX and to reread it each time the prescription is renewed.

Osteoporosis Recommendations, Including Calcium and Vitamin D Supplementation

Instruct patients to take supplemental calcium and vitamin D, if daily dietary intake is inadequate. Weight-bearing exercise should be considered along with the modification of certain behavioral factors, such as cigarette smoking and/or excessive alcohol consumption, if these factors exist.

Dosing Instructions

Instruct patients that the expected benefits of FOSAMAX may only be obtained when it is taken with plain water the first thing upon arising for the day at least 30 minutes before the first food, beverage, or medication of the day. Even dosing with orange juice or coffee has been shown to markedly reduce the absorption of FOSAMAX [see Clinical Pharmacology (12.3)].

Instruct patients not to chew or suck on the tablet because of a potential for oropharyngeal ulceration.

Instruct patients to swallow each tablet of FOSAMAX with a full glass of water (6-8 ounces) to facilitate delivery to the stomach and thus reduce the potential for esophageal irritation. Instruct patients to drink at least 2 ounces (a quarter of a cup) of water after taking FOSAMAX oral solution, to facilitate gastric emptying.

Instruct patients not to lie down for at least 30 minutes and until after their first food of the day.

Instruct patients not to take FOSAMAX at bedtime or before arising for the day. Patients should be informed that failure to follow these instructions may increase their risk of esophageal problems.

Instruct patients that if they develop symptoms of esophageal disease (such as difficulty or pain upon swallowing, retrosternal pain or new or worsening heartburn) they should stop taking FOSAMAX and consult their physician.

If patients miss a dose of once weekly FOSAMAX, instruct patients to take one dose on the morning after they remember. They should not take two doses on the same day but should return to taking one dose once a week, as originally scheduled on their chosen day.

Distributed by: Organon LLC, a subsidiary of
ORGANON & Co.,
Jersey City, NJ 07302, USA

For patent information: www.organon.com/our-solutions/patent/

© 2026 Organon group of companies. All rights reserved.

uspi-og0217-mf-2602r001

MEDICATION GUIDE
FOSAMAX® (FOSS-ah-max)
(alendronate sodium)
Tablets

Read the Medication Guide that comes with FOSAMAX® before you start taking it and each time you get a refill. There may be new information. This Medication Guide does not take the place of talking with your doctor about your medical condition or treatment. Talk to your doctor if you have any questions about FOSAMAX.

What is the most important information I should know about FOSAMAX?

FOSAMAX can cause serious side effects including:

1. Esophagus problems
2. Low calcium levels in your blood (hypocalcemia)
3. Bone, joint, or muscle pain
4. Severe jaw bone problems (osteonecrosis)
5. Unusual breaks in thigh and other bones

1. Esophagus problems.
  Some people who take FOSAMAX may develop problems in the esophagus (the tube that connects the mouth and the stomach). These problems include irritation, inflammation, or ulcers of the esophagus which may sometimes bleed.
  - It is important that you take FOSAMAX exactly as prescribed to help lower your chance of getting esophagus problems. (See the section "How should I take FOSAMAX?")
  - Stop taking FOSAMAX and call your doctor right away if you get chest pain, new or worsening heartburn, or have trouble or pain when you swallow.
2. Low calcium levels in your blood (hypocalcemia).
  FOSAMAX may lower the calcium levels in your blood. If you have low blood calcium before you start taking FOSAMAX, it may get worse during treatment. Your low blood calcium must be treated before you take FOSAMAX. Most people with low blood calcium levels do not have symptoms, but some people may have symptoms. Call your doctor right away if you have symptoms of low blood calcium such as:
  - Spasms, twitches, or cramps in your muscles
  - Numbness or tingling in your fingers, toes, or around your mouth
  Your doctor may prescribe calcium and vitamin D to help prevent low calcium levels in your blood, while you take FOSAMAX. Take calcium and vitamin D as your doctor tells you to.
3. Bone, joint, or muscle pain.
  Some people who take FOSAMAX develop severe bone, joint, or muscle pain.
4. Severe jaw bone problems (osteonecrosis).
  Severe jaw bone problems may happen when you take FOSAMAX. Your doctor should examine your mouth before you start FOSAMAX. Your doctor may tell you to see your dentist before you start FOSAMAX. It is important for you to practice good mouth care during treatment with FOSAMAX.
5. Unusual breaks in thigh and other bones.
  Some people have had unusual bone breaks, including thigh bone when taking FOSAMAX. A break in the thigh bone can feel like a new pain in your hip, groin, or thigh. People taking FOSAMAX can also have breaks in other bones.

Call your doctor right away if you have any of these side effects.

What is FOSAMAX?

FOSAMAX is a prescription medicine used to:

- Treat or prevent osteoporosis in women after menopause. It helps reduce the chance of having a hip or spinal fracture (break).
- Increase bone mass in men with osteoporosis.
- Treat osteoporosis in either men or women who are taking corticosteroid medicines.
- Treat certain men and women who have Paget's disease of the bone.

It is not known how long FOSAMAX works for the treatment and prevention of osteoporosis. You should see your doctor regularly to determine if FOSAMAX is still right for you.

FOSAMAX is not for use in children.

Who should not take FOSAMAX?

Do not take FOSAMAX if you:

- Have certain problems with your esophagus, the tube that connects your mouth with your stomach
- Cannot stand or sit upright for at least 30 minutes
- Have low levels of calcium in your blood
- Are allergic to FOSAMAX or any of its ingredients. A list of ingredients is at the end of this leaflet.

What should I tell my doctor before taking FOSAMAX?

Before you start FOSAMAX, be sure to talk to your doctor if you:

- Have problems with swallowing
- Have stomach or digestive problems
- Have low blood calcium
- Plan to have dental surgery or teeth removed
- Have kidney problems
- Have been told you have trouble absorbing minerals in your stomach or intestines (malabsorption syndrome)
- Are pregnant, trying to become pregnant or suspect that you are pregnant. If you become pregnant while taking FOSAMAX, stop taking it and contact your doctor. It is not known if FOSAMAX can harm your unborn baby.
- Are breast-feeding or plan to breast-feed. It is not known if FOSAMAX passes into your milk and may harm your baby.

Especially tell your doctor if you take:

- antacids
- aspirin
- Nonsteroidal Anti-Inflammatory (NSAID) medicines

Tell your doctor about all the medicines you take, including prescription and non-prescription medicines, vitamins, and herbal supplements. Certain medicines may affect how FOSAMAX works.

Know the medicines you take. Keep a list of them and show it to your doctor and pharmacist each time you get a new medicine.

How should I take FOSAMAX?

- Take FOSAMAX exactly as your doctor tells you.
- FOSAMAX works only if taken on an empty stomach.
- Take FOSAMAX, after you get up for the day and before taking your first food, drink, or other medicine.
- Take FOSAMAX while you are sitting or standing.
- Do not chew or suck on a tablet of FOSAMAX.
- Swallow FOSAMAX tablet with a full glass (6-8 oz) of plain water only.
- Do not take FOSAMAX with mineral water, coffee, tea, soda, or juice.
  - If you take Alendronate Daily:
    - Take 1 alendronate tablet one time a day, every day after you get up for the day and before taking your first food, drink, or other medicine.
  - If you take Once Weekly FOSAMAX:
    - Choose the day of the week that best fits your schedule.
    - Take 1 dose of FOSAMAX every week on your chosen day after you get up for the day and before taking your first food, drink, or other medicine.

After swallowing FOSAMAX tablet, wait at least 30 minutes:

- Before you lie down. You may sit, stand or walk, and do normal activities like reading.
- Before you take your first food or drink except for plain water.
- Before you take other medicines, including antacids, calcium, and other supplements and vitamins.

Do not lie down for at least 30 minutes after you take FOSAMAX and after you eat your first food of the day.

If you miss a dose of FOSAMAX, do not take it later in the day. Take your missed dose on the next morning after you remember and then return to your normal schedule. Do not take 2 doses on the same day.

If you take too much FOSAMAX, call your doctor. Do not try to vomit. Do not lie down.

What are the possible side effects of FOSAMAX?

FOSAMAX may cause serious side effects.

- See "What is the most important information I should know about FOSAMAX?"

The most common side effects of FOSAMAX are:

- Stomach area (abdominal) pain
- Heartburn
- Constipation
- Diarrhea
- Upset stomach
- Pain in your bones, joints, or muscles
- Nausea

You may get allergic reactions, such as hives or swelling of your face, lips, tongue, or throat.

Worsening of asthma has been reported.

Tell your doctor if you have any side effect that bothers you or that does not go away.

These are not all the possible side effects of FOSAMAX. For more information, ask your doctor or pharmacist.

Call your doctor for medical advice about side effects. You may report side effects to FDA at 1-800-FDA-1088.

How do I store FOSAMAX?

- Store FOSAMAX at room temperature, 59°F to 86°F (15°C to 30°C).
- Keep FOSAMAX in a tightly closed container.

Keep FOSAMAX and all medicines out of the reach of children.

General information about the safe and effective use of FOSAMAX.

Medicines are sometimes prescribed for purposes other than those listed in a Medication Guide. Do not use FOSAMAX for a condition for which it was not prescribed. Do not give FOSAMAX to other people, even if they have the same symptoms you have. It may harm them.

This Medication Guide summarizes the most important information about FOSAMAX. If you would like more information, talk with your doctor. You can ask your doctor or pharmacist for information about FOSAMAX that is written for health professionals.

What are the ingredients in FOSAMAX?

Tablets:

Active ingredient: alendronate sodium

Inactive ingredients: microcrystalline cellulose, anhydrous lactose, croscarmellose sodium, magnesium stearate.

Distributed by: Organon LLC, a subsidiary of
ORGANON & Co.,
Jersey City, NJ 07302, USA

For patent information: www.organon.com/our-solutions/patent/

© 2026 Organon group of companies. All rights reserved.

Revised: 2/2026

usmg-og0217-mf-2602r001

This Medication Guide has been approved by the U.S. Food and Drug Administration.

PRINCIPAL DISPLAY PANEL - 4 Tablet Blister Pack

ONCE WEEKLY
FOSAMAX® 70 mg
(Alendronate Sodium Tablets)

Dispense the enclosed
Medication Guide
to each patient.

Each tablet contains
91.37 mg
alendronate sodium
(70 mg free acid
equivalent)

4 Tablets

Rx only

USUAL ADULT
DOSAGE:
ONE 70 mg TABLET
ONCE WEEKLY

See accompanying
circular for complete
dosage information.

Dist. by:
Organon LLC, a subsidiary of
ORGANON & Co.,
Jersey City, NJ 07302, USA

Manuf. by:
Savio Industrial S.r.L.
Pavia, Italy.

Alendronate Sodium (active ingred.) Made in Ireland.

Formulated in Italy.

Copyright © 2021 Organon Global Inc.
All rights reserved.